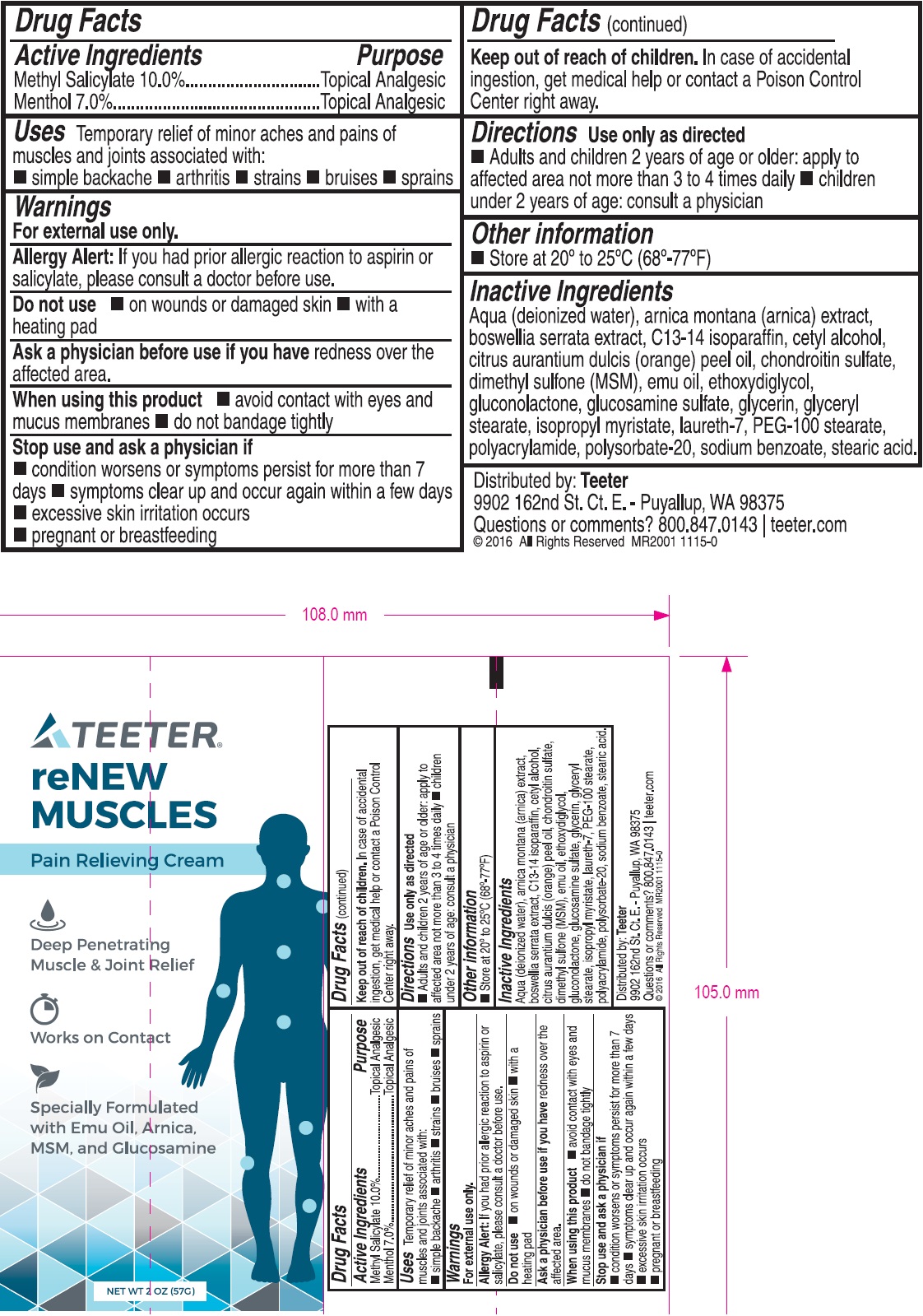 DRUG LABEL: Teeter reNEW MUSCLES Pain Relieving
NDC: 70329-717 | Form: CREAM
Manufacturer: STL International INC
Category: otc | Type: HUMAN OTC DRUG LABEL
Date: 20231110

ACTIVE INGREDIENTS: METHYL SALICYLATE 10 mg/1 g; MENTHOL 7 mg/1 g
INACTIVE INGREDIENTS: WATER; ARNICA MONTANA; INDIAN FRANKINCENSE; C13-14 ISOPARAFFIN; CETYL ALCOHOL; ORANGE OIL; DIMETHYL SULFONE; EMU OIL; DIETHYLENE GLYCOL MONOETHYL ETHER; GLUCONOLACTONE; GLUCOSAMINE SULFATE; GLYCERIN; GLYCERYL MONOSTEARATE; ISOPROPYL MYRISTATE; LAURETH-7; PEG-100 STEARATE; POLYSORBATE 20; SODIUM BENZOATE; STEARIC ACID

Teeter reNEW MUSCLES Pain Relieving Cream

Active Ingredients

Methyl Salicylate 10.0%

Menthol 7.0%

Purpose

Topical Analgesic

Uses

Temporary relief of minor aches and pains of muscles and joints associated with:

• simple backache • arthritis • strains • bruises • sprains

Warnings

For external use only.

Allergy Alert:

If you had prior allergic reaction to aspirin or salicylate, please consult a doctor before use.

Do not use

• on wounds or damaged skin • with a heating pad

Ask a physician before use if you have

redness over the affected area.

When using this product

• avoid contact with eyes and mucus membranes • do not bandage tightly

Stop use and ask a physician if

• condition worsens or symptoms persist for more than 7 days • symptoms clear up and occur again within a few days • excessive skin irritation occurs • pregnant or breastfeeding

Keep out of reach of children.

In case of accidental ingestion, get medical help or contact a Poison Control Center right away.

Use only as directed Directions

• Adults and children 2 years of age or older: apply to affected area not more than 3 to 4 times daily • children under 2 years of age: consult a physician

Other information

Store at 20° to 25°C (68°-77°F)

Inactive Ingredients

Aqua (deionized water), arnica montana (arnica) extract, boswellia serrata extract, C13-14 isoparaffin, cetyl alcohol, citrus aurantium dulcis (orange) peel oil, chondroitin sulfate, dimethyl sulfone (MSM), emu oil, ethoxydiglycol, gluconolactone, glucosamine sulfate, glycerin, glyceryl stearate, isopropyl myristate, laureth-7, PEG-100 stearate, polyacrylamide, polysorbate-20, sodium benzoate, stearic acid